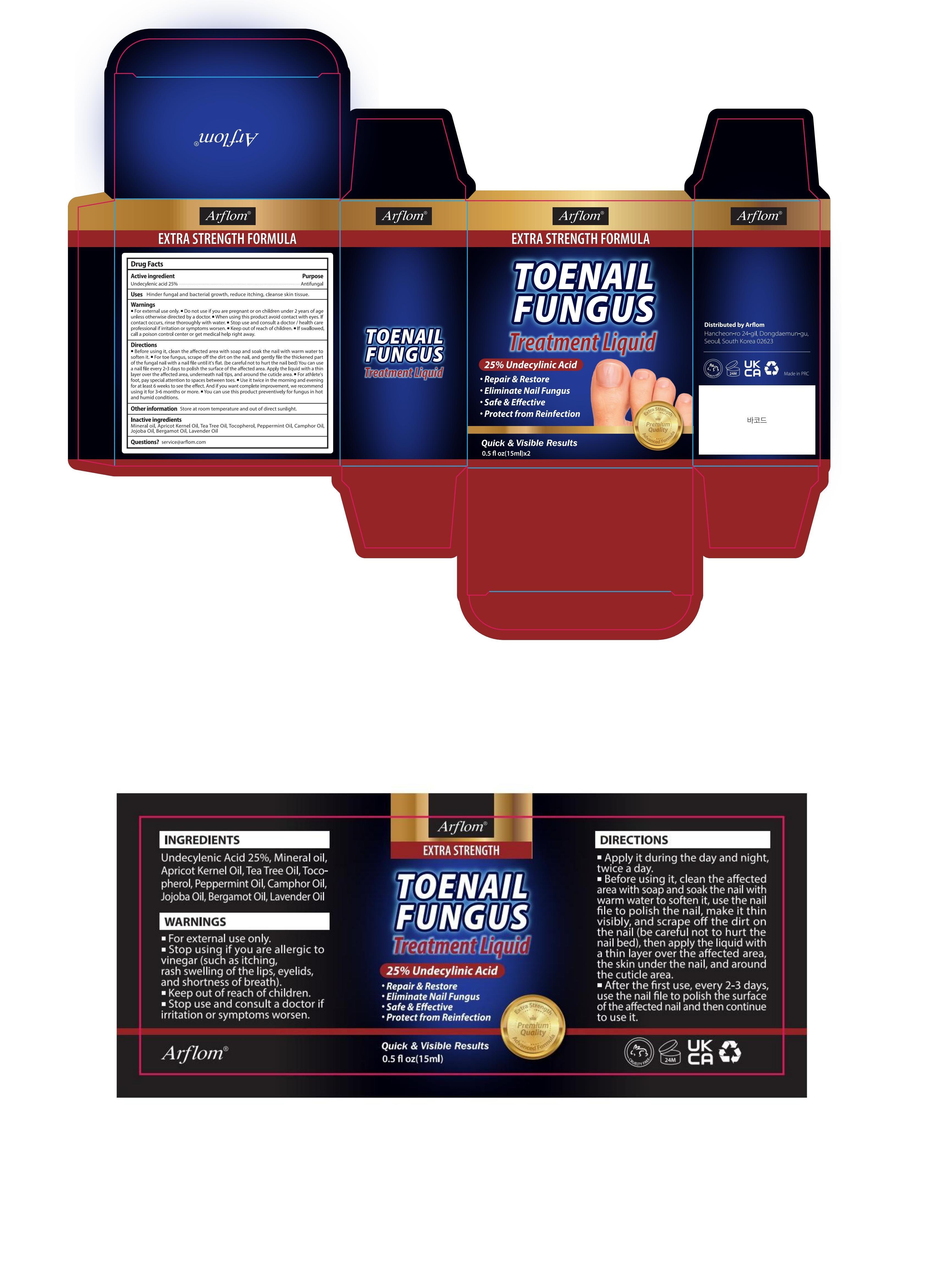 DRUG LABEL: Arflom Toenail Fungus Treatment Liquid
NDC: 85817-006 | Form: LIQUID
Manufacturer: Guangzhou Qiexiran Cosmetics Co., Ltd.
Category: otc | Type: HUMAN OTC DRUG LABEL
Date: 20251015

ACTIVE INGREDIENTS: UNDECYLENIC ACID 25 g/100 mL
INACTIVE INGREDIENTS: BERGAMOT OIL; JOJOBA OIL; TOCOPHEROL; CAMPHOR OIL; PEPPERMINT OIL; LAVENDER OIL; MINERAL OIL; APRICOT KERNEL OIL; TEA TREE OIL

85817-006

Active Ingredient

Undecylenic acid 25%

Purpose

Antifungal

Use

Hinder fungal and bacterial growth, reduce itching, cleanse skin tissue.

Warnings

For external use only.

Do not use

■ if you are pregnant
■ if you are allergic to vinegar (such as itching, rash swelling of the lips, eyelids, and shortness of breath).
■ on children under 2 years of age unless otherwise directed by a doctor.

When Using

■ avoid contact with eyes. If contact occurs, rinse thoroughly with water.

Stop Use

and consult a doctor / health care professional if
irritation or symptoms worsen.

Keep Out Of Reach Of Children

If swallowed, call a poison control centre or get medical help right away.

Directions

■ Before using it, clean the affected area with soap and soak the nail with warm water to soften it.
■ For toe fungus,
- scrape off the dirt on the nail, and gently file the thickened part of the fungal nail with a nail file until it's flat. (be careful not to hurt the nail bed)
-You can use a nail file every 2-3 days to polish the surface of the affected area.
-Apply the liquid with a thin layer over the affected area, the skin under the nail, and around the cuticle area.
■ For athlete's foot, pay special attention to spaces between toes.
■ Use it twice daily, in the morning and evening, for at least 6 weeks to see results. For complete improvement, we recommend using it for 3 to 6 months or longer.
■ You can use this product preventively for fungus in hot and humid conditions.

Other information

Store at room temperature and out of direct sunlight.

Inactive ingredients

Mineral oil, Apricot Kernel Oil, Tea Tree Oil,Tocopherol, Peppermint Oil, Camphor Oil, Jojoba Oil, Bergamot Oil, Lavender Oil

Questions

Visit : Arflom.com email to service@arflom.com